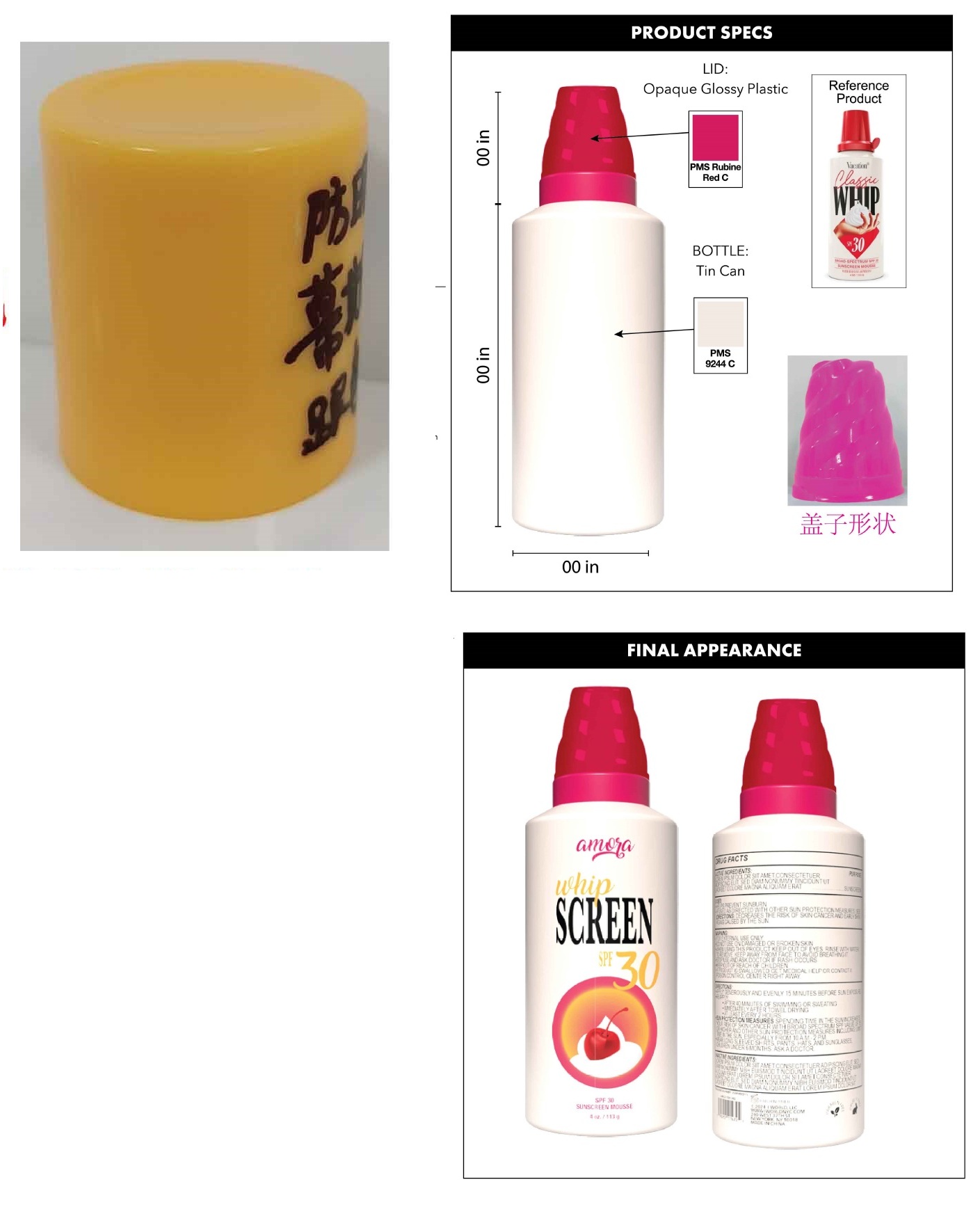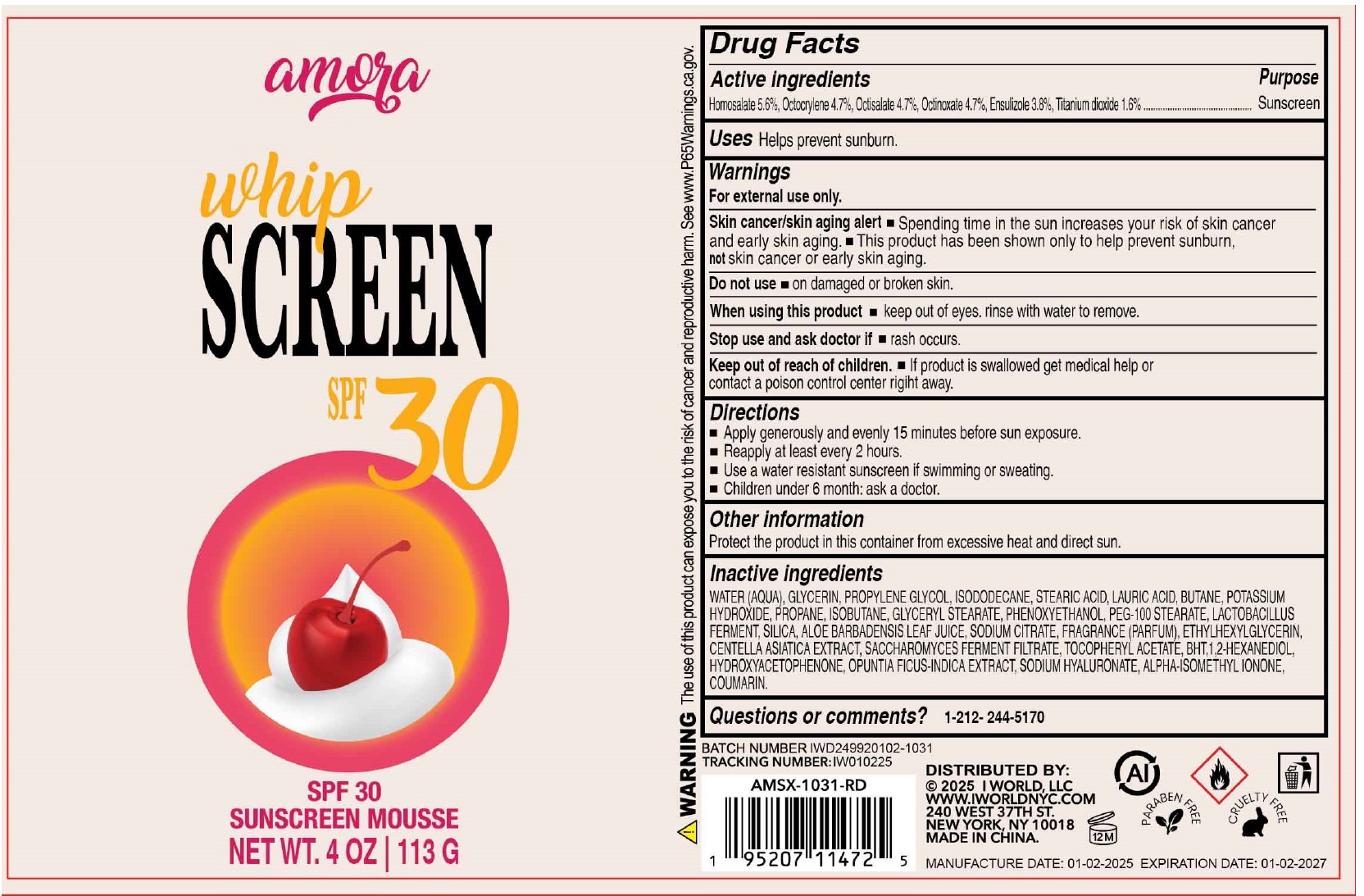 DRUG LABEL: Amora Whip Screen SPF 30
NDC: 85179-000 | Form: AEROSOL, FOAM
Manufacturer: I World LLC
Category: otc | Type: HUMAN OTC DRUG LABEL
Date: 20250120

ACTIVE INGREDIENTS: HOMOSALATE 56 mg/1 g; OCTOCRYLENE 47 mg/1 g; OCTISALATE 47 mg/1 g; OCTINOXATE 47 mg/1 g; ENSULIZOLE 38 mg/1 g; TITANIUM DIOXIDE 16 mg/1 g
INACTIVE INGREDIENTS: WATER; GLYCERIN; PROPYLENE GLYCOL; ISODODECANE; STEARIC ACID; LAURIC ACID; BUTANE; POTASSIUM HYDROXIDE; PROPANE; ISOBUTANE; GLYCERYL STEARATE; PHENOXYETHANOL; PEG-100 STEARATE; SILICON DIOXIDE; ALOE VERA LEAF; SODIUM CITRATE; ETHYLHEXYLGLYCERIN; CENTELLA ASIATICA TRITERPENOIDS; .ALPHA.-TOCOPHEROL ACETATE; BUTYLATED HYDROXYTOLUENE; 1,2-HEXANEDIOL; HYDROXYACETOPHENONE; OPUNTIA FICUS-INDICA WHOLE; SODIUM HYALURONATE; ISOMETHYL-.ALPHA.-IONONE; COUMARIN

Amora Whip Screen SPF 30

Active ingredients

Homosalate 5.6%, Octocrylene 4.7%, Octisalate 4.7%, Octinoxate 4.7%, Ensulizole 3.8%, Titanium dioxide 1.6%.

Purpose

Sunscreen

Uses

Helps prevent sunburn.

Warnings

For external use only.

Skin cancer/skin aging alert • Spending time in the sun increases your risk of skin cancer and early skin aging.

• This product has been shown only to help prevent sunburn, not skin cancer or early skin aging.

Do not use

- on damaged or broken skin.

When using this product

- Keep out of eyes. rinse with water to remove.

Stop use and ask doctor if

- rash occurs.

Keep out of reach of children.

- If product is swallowed, get medical help or contact a Poison Control Center right away.

Directions

- Apply generously and evenly 15 minutes before sun exposure.
- Reapply at least every 2 hours.
- Use a water resistant sunscreen if swimming or sweating.
- Children under 6 month: ask a doctor.

Other information

Protect the product in this container from excessive heat and direct sun.

Inactive ingredients

WATER (AQUA), GLYCERIN, PROPYLENE GLYCOL, ISODODECANE, STEARIC ACID, LAURIC ACID, BUTANE, POTASSIUM HYDROXIDE, PROPANE, ISOBUTANE, GLYCERYL STEARATE, PHENOXYETHANOL, PEG-100 STEARATE, LACTOBACILLUS FERMENT, SILICA, ALOE BARBADENSIS LEAF JUICE, SODIUM CITRATE, FRAGRANCE (PARFUM), ETHYLHEXYLGLYCERIN, CENTELLA ASIATICA EXTRACT, SACCHAROMYCES FERMENT FILTRATE, TOCOPHERYL ACETATE, BHT, 1,2-HEXANEDIOL, HYDROXYACETOPHENONE, OPUNTIA FICUS-INDICA EXTRACT, SODIUM HYALURONATE, ALPHA- ISOMETHYL IONONE, COUMARIN.

Questions or comments?

1-212-244-5170